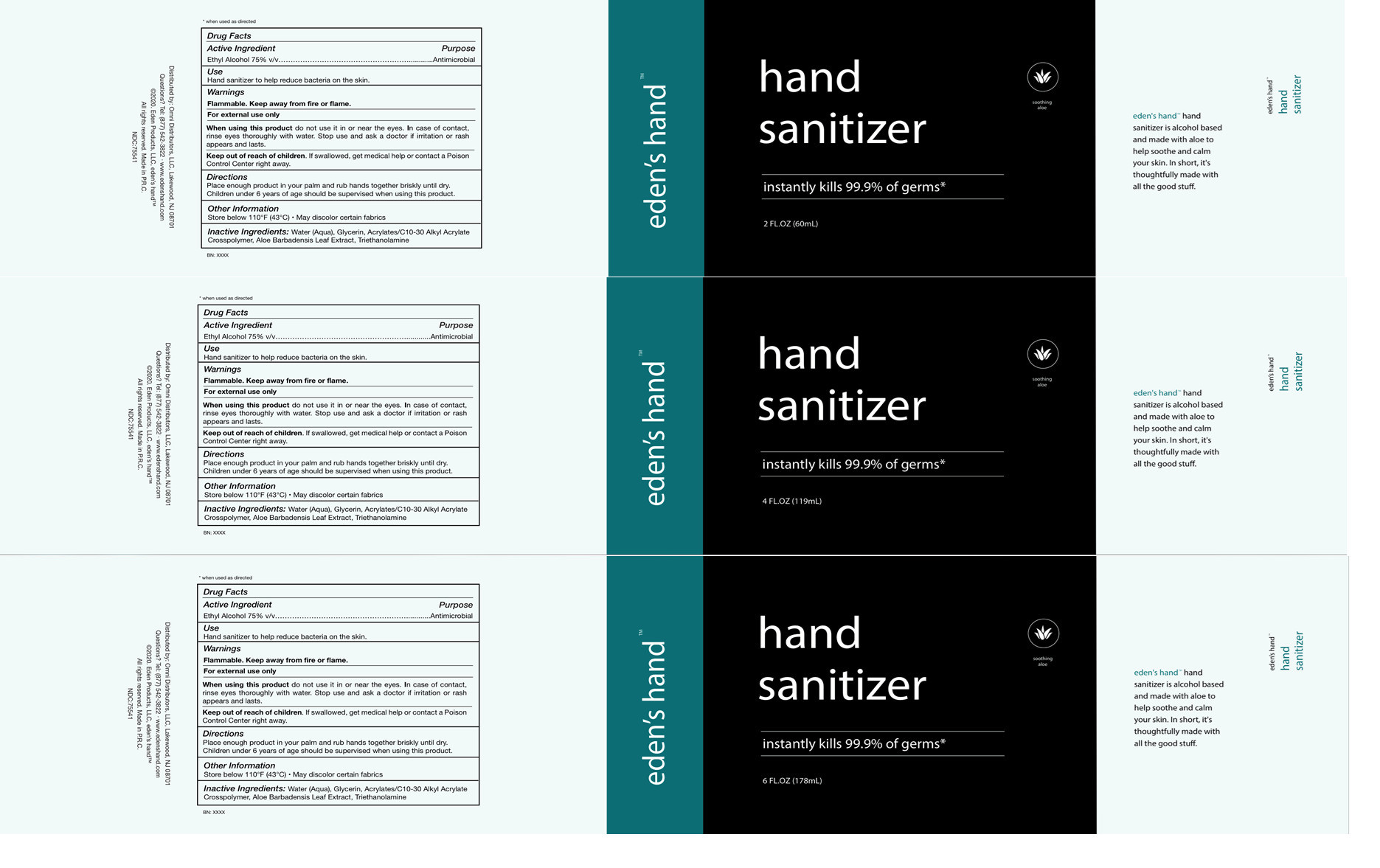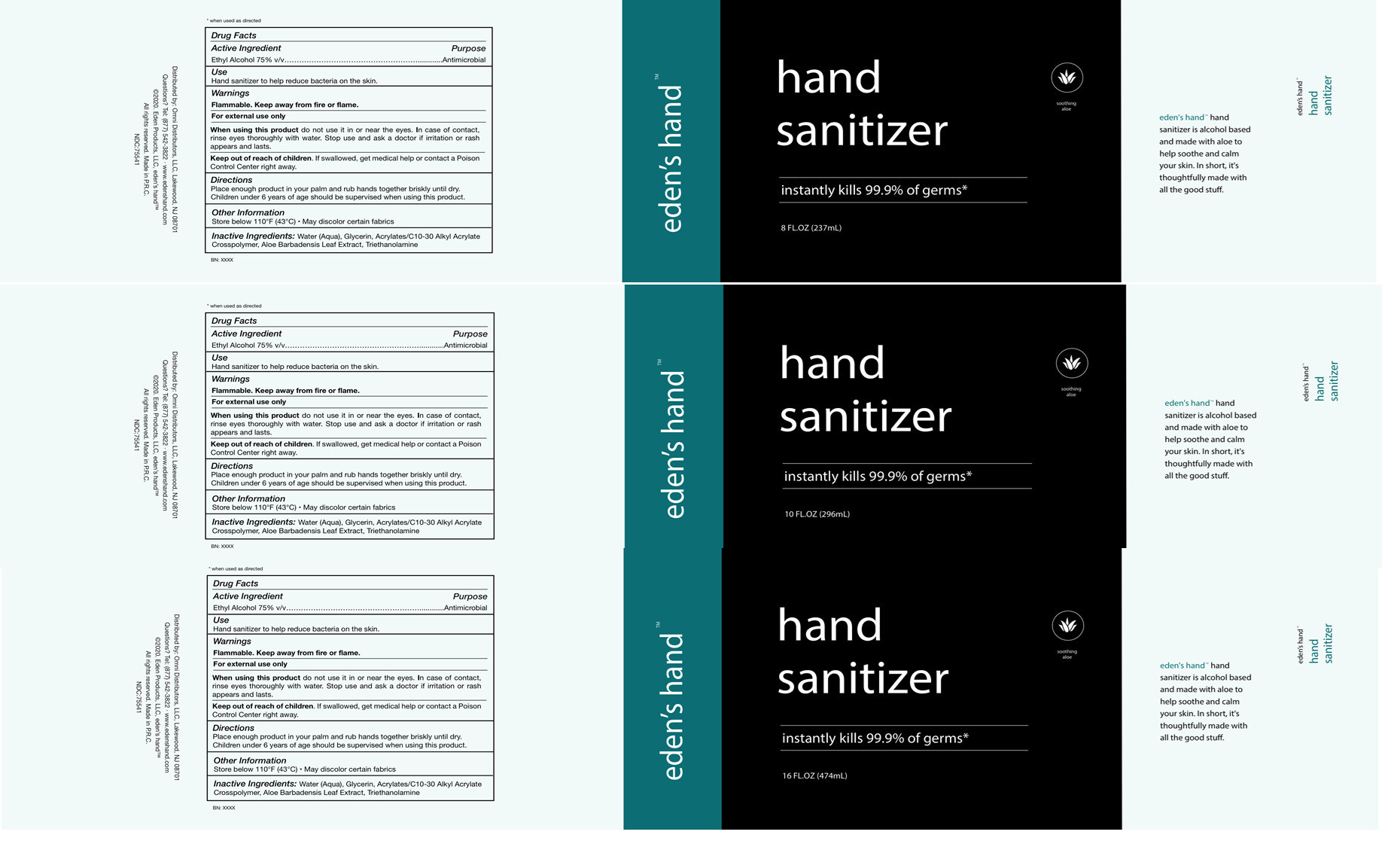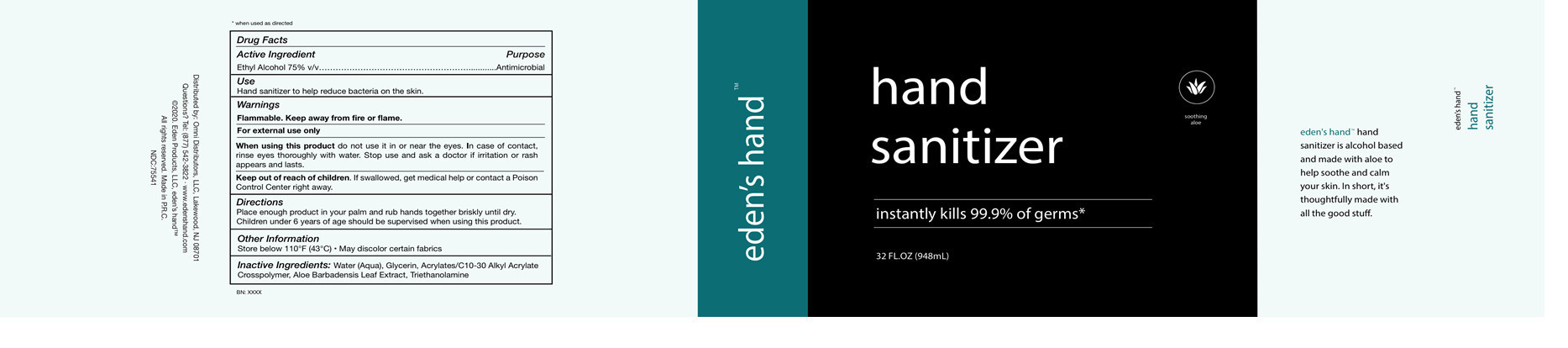 DRUG LABEL: Hand Sanitizer
NDC: 75541-006 | Form: GEL
Manufacturer: Ningbo Meiteli Cosmetic Co., Ltd.
Category: otc | Type: HUMAN OTC DRUG LABEL
Date: 20200514

ACTIVE INGREDIENTS: ALCOHOL 75 mL/100 mL
INACTIVE INGREDIENTS: TROLAMINE; GLYCERIN; WATER; ALOE; CARBOMER INTERPOLYMER TYPE A (55000 CPS)

Advanced Hand Sanitizer

Active Ingredient(s)

Ethyl Alcohol 75%

Purpose

Antimicrobial

Use

Hand Sanitizer to help reduce bacteria on the skin.

Warning

Flammable. Keep away from heat or flame

For external use only.

Do not use near eyes

In case of contact rinse eyes thoroughly with water.

Stop use

Stop use and see a doctor if imtation or rash appears and lasts

Keep out of reach of children. If swallowed, get medical help or contact a poison control Center right away.

Directions

Put enough sanitizer in your palm to cover both hands,Rub hands together brishly until dry,Children under six should be supervised

Other

- Store below 110F(43C)
- May discolor some fabrics or surfaces

Inactive ingredients

Water(Aqua). Glycerin, Acrylatewc10-30 Alkyl CrateCrosspolymer, Aloe Barbadensis Loaf Extract, Triethanolamine